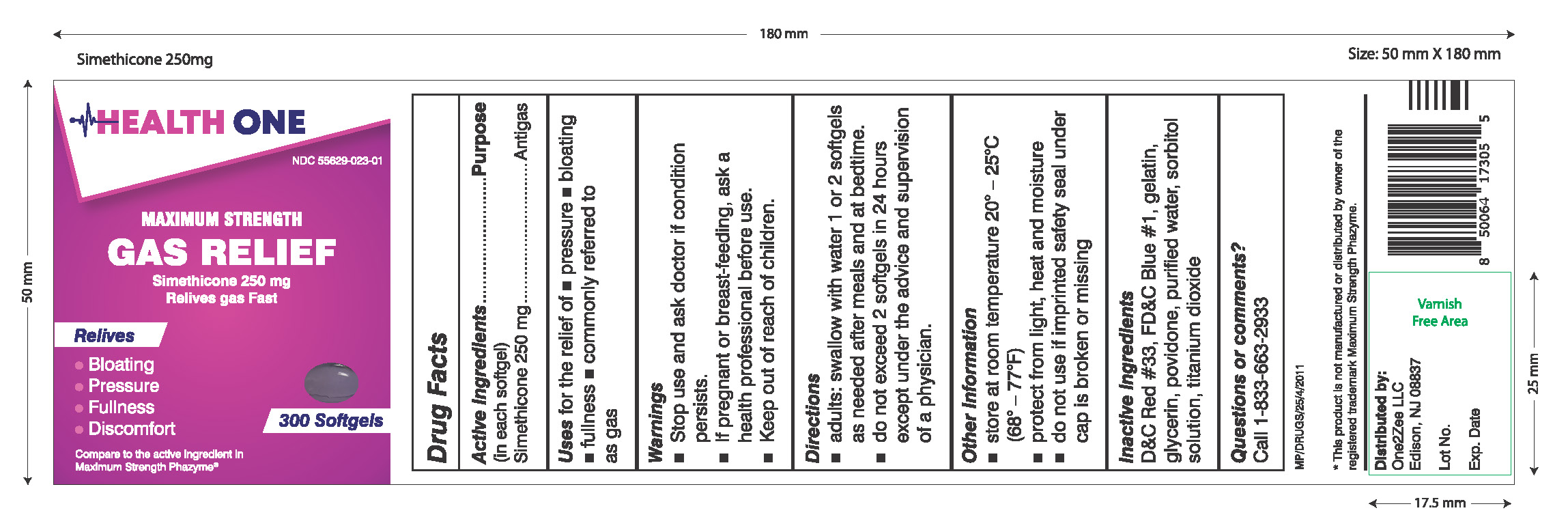 DRUG LABEL: Simethicone 250MG Maximum Strength Gas Relief
NDC: 55629-023 | Form: CAPSULE, LIQUID FILLED
Manufacturer: One2Zee Limited Liability Company
Category: otc | Type: HUMAN OTC DRUG LABEL
Date: 20240924

ACTIVE INGREDIENTS: DIMETHICONE 250 mg/1 1
INACTIVE INGREDIENTS: D&C RED NO. 33; FD&C BLUE NO. 1; GELATIN; GLYCERIN; POVIDONE; WATER; SORBITOL SOLUTION; TITANIUM DIOXIDE

Simethicone 250mg Maximum Strength Gas Relief

Active Ingredients (in each softgel)

Simethicone 250 mg

Purpose

Antigas

INDICATIONS AND USAGE

Use for the relief of

- pressure
- bloating
- fullness
- commonly referred to as gas

Warning

- Stop use and ask doctor if condition persists.
- If pregnant or breast-feeding, ask a health professional before use.

Directions

- adults:swallow with water 1 or 2 softgels as needed after meals and at bedtime
- do not exceed 4 softgels in 24 hours except under the advice and supervision of a physician

Other Information

- store at controlled room temperature 20°-25°C (68°-77°F)
- protact from light, heat and moisture
- do not use if imprinted safety seal under cap is broken or missing

INACTIVE INGREDIENT

D&C Red #33, FD&C Blue #1, gelatin, glycerin, povidone, purified water, sorbitol solution, titanium dioxide

Questions or comments?
Call 1-833-663-2933